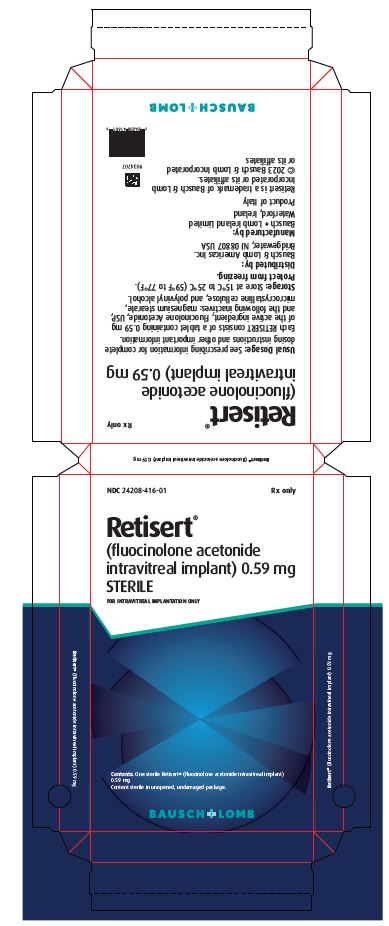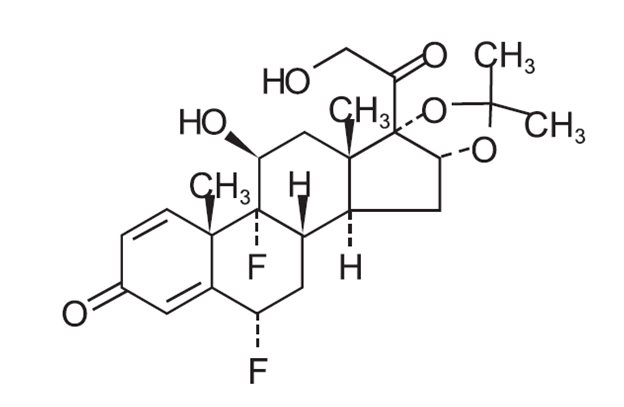 DRUG LABEL: Retisert
NDC: 24208-416 | Form: IMPLANT
Manufacturer: Bausch & Lomb Incorporated
Category: prescription | Type: HUMAN PRESCRIPTION DRUG LABEL
Date: 20250414

ACTIVE INGREDIENTS: FLUOCINOLONE ACETONIDE 0.59 mg/1 1
INACTIVE INGREDIENTS: MAGNESIUM STEARATE; MICROCRYSTALLINE CELLULOSE; POLYVINYL ALCOHOL, UNSPECIFIED

HIGHLIGHTS OF PRESCRIBING INFORMATION

These highlights do not include all the information needed to use RETISERT safely and effectively. See full prescribing information for RETISERT.
RETISERT (fluocinolone acetonide intravitreal implant) 0.59 mg,
for intravitreal use
Initial U.S. Approval: 1963

1 INDICATIONS AND USAGE

RETISERT is a corticosteroid indicated for the treatment of chronic noninfectious uveitis affecting the posterior segment of the eye. (1)

2 DOSAGE AND ADMINISTRATION

- RETISERT is surgically implanted into the posterior segment of the affected eye through a pars plana incision. (2.1)
- RETISERT is designed to release fluocinolone acetonide at a nominal initial rate of 0.6 mcg/day, decreasing over the first month to a steady state between 0.3-0.4 mcg/day over approximately 30 months. (2.1)
- Aseptic technique should be maintained at all times prior to and during the surgical implantation procedure. (2.2)

3 DOSAGE FORMS AND STRENGTHS

1. 0.59 mg fluocinolone acetonide intravitreal implant. (3)

4 CONTRAINDICATIONS

1. Surgical placement of RETISERT is contraindicated in active viral, bacterial, mycobacterial and fungal infections of ocular structures. (4.1)

5 WARNINGS AND PRECAUTIONS

- Cataract formation: Nearly all phakic patients are expected to develop cataracts and require cataract surgery. (5.1)
- Endophthalmitis: Late onset endophthalmitis has been observed. (5.2)
- Increase in intraocular pressure: Use of corticosteroids may result in elevated IOP and/or glaucoma. (5.3)IOP lowering medications were required in > 75% of patients; filtering surgeries were required in > 35% of patients. (6.1)
- Separation of implant components: Physicians should periodically monitor the integrity of the implant by visual inspection. (5.4)

6 ADVERSE REACTIONS

- Ocular adverse events included procedural complications, and eye pain (> 50%). Thirty-five to forty percent of patients reported ocular/conjunctival hyperemia, reduced visual acuity, and conjunctival hemorrhage. (6.1)
- The most common non-ocular event reported was headache (33%). (6.2)

To report SUSPECTED ADVERSE REACTIONS, contact Bausch & Lomb Incorporated at 1-800-553-5340 or FDA at 1-800-FDA-1088 or www.fda.gov/medwatch.

FULL PRESCRIBING INFORMATION

1 INDICATIONS AND USAGE

RETISERT®is indicated for the treatment of chronic non-infectious uveitis affecting the posterior segment of the eye.

2 DOSAGE AND ADMINISTRATION

2.1 Dosing Information

RETISERT is implanted into the posterior segment of the affected eye through a pars plana incision.

The implant contains one tablet of 0.59 mg of fluocinolone acetonide. RETISERT is designed to release fluocinolone acetonide at a nominal initial rate of 0.6 mcg/day, decreasing over the first month to a steady state between

0.3-0.4 mcg/day over approximately 30 months. Following depletion of fluocinolone acetonide as evidenced by recurrence of uveitis, RETISERT may be replaced.

2.2 Handling of Implant

Caution should be exercised in handling RETISERT in order to avoid damage to the implant, which may result in an increased rate of drug release from the implant. Thus, RETISERT should be handled only by the suture tab. Care should be taken during implantation and explantation to avoid sheer forces on the implant that could disengage the silicone cup reservoir (which contains a fluocinolone acetonide tablet) from the suture tab. Aseptic technique should be maintained at all times prior to and during the surgical implantation procedure.

RETISERT should not be resterilized by any method.

3 DOSAGE FORMS AND STRENGTHS

0.59 mg fluocinolone acetonide intravitreal implant.

4 CONTRAINDICATIONS

4.1 Viral, Bacterial, Mycobacterial and Fungal Infections of Ocular Structures

Surgical placement of RETISERT is contraindicated in active viral diseases of the cornea and conjunctiva including epithelial herpes simplex keratitis (dendritic keratitis), vaccinia, and varicella, and also in active bacterial, mycobacterial or fungal infections of the eye.

5 WARNINGS AND PRECAUTIONS

5.1 Cataract Formation

Use of corticosteroids may result in posterior subcapsular cataract formation. Based on clinical trials with RETISERT, during the 3-year post-implantation period, nearly all phakic eyes are expected to develop cataracts and require cataract surgery.

5.2 Endophthalmitis and Surgical Complications

Late onset endophthalmitis has been observed. These events are often related to the integrity of the surgical wound site. Careful attention to assure tight closure of the scleral wound and the integrity of the overlying conjunctiva at the wound site is important.

Potential complications accompanying intraocular surgery to place RETISERT into the vitreous cavity may include, but are not limited to, the following: cataract formation, choroidal detachment, endophthalmitis, hypotony, increased intraocular pressure, exacerbation of intraocular inflammation, retinal detachment, vitreous hemorrhage, vitreous loss, and wound dehiscence.

Following implantation of RETISERT, nearly all patients will experience an immediate and temporary decrease in visual acuity in the implanted eye which lasts for approximately one to four weeks post-operatively.

5.3 Increase in Intraocular Pressure

Prolonged use of corticosteroids may result in elevated IOP and/or glaucoma with damage to the optic nerve, defects in visual acuity and fields of vision. Steroids should be used with caution in the presence of glaucoma. Patients must be monitored for elevated IOP.

Based on clinical trials with RETISERT, within 3-years post-implantation, approximately 77% of patients will require IOP lowering medications to control intraocular pressure and 37% of patients will require filtering procedures to control intraocular pressure [see Adverse Reactions (6.1)] .

5.4 Separation of Implant Components

In vitro stability studies show that the strength of the adhesive bond between the silicone cup reservoir and the suture tab is reduced with prolonged hydration, indicating a potential for the separation of these components. The suture tab composition is a silicone elastomer reinforced with a polyester mesh. Physicians should periodically monitor the integrity of the implant by visual inspection.

5.5 Other Corticosteroid Induced Adverse Reactions

RETISERT should be used with caution in patients with a history of a viral, bacterial, mycobacterial or fungal infection of the cornea and conjunctiva including epithelial herpes simplex keratitis (dendritic keratitis), vaccinia and varicella. Use of ocular steroids may prolong the course and may exacerbate the severity of many viral infections of the eye (including herpes simplex). Employment of a corticosteroid medication in the treatment of patients with a history of herpes simplex requires great caution.

Prolonged use of corticosteroids may suppress the host response and thus increase the hazard of secondary ocular infections (bacterial, fungal, and viral). In acute purulent conditions of the eye, steroids may mask infection or enhance existing infection. Fungal and viral infections of the cornea are particularly prone to develop coincidentally with long-term application of steroids. The possibility of fungal invasion should be considered in any persistent corneal ulceration where steroid treatment has been used.

Since resistance to infections is known to be reduced by corticosteroids, simultaneous bilateral implantation should not be carried out, in order to limit the potential for bilateral post-operative infection.

Ocular administration of corticosteroids has also been associated with delayed wound healing and perforation of the globe where there is thinning of the sclera.

The use of steroids after cataract surgery may delay healing and increase the incidence of bleb formation.

6 ADVERSE REACTIONS

6.1 Clinical Trials Experience - Ocular Events

The available safety data includes exposure to RETISERT in patients with chronic non-infectious uveitis affecting the posterior segment in two multicenter controlled clinical trials. Patients were randomized to dosage regimens of 0.59 mg or 2.1 mg implants.

The most frequently reported ocular adverse events were cataract, increased intraocular pressure, procedural complication, and eye pain. These events occurred in approximately 50 - 90% of patients. Cataract includes aggravated cataract, and posterior capsular opacification. Procedural complications includes post-op complication, post-op wound complication, post-op wound site erythema, and wound dehiscense.

Based on clinical trials with RETISERT, during the 3-year post-implantation period, nearly all phakic eyes are expected to develop cataracts and require cataract surgery. IOP lowering medications to lower intraocular pressure were required in approximately 77% of patients; filtering surgeries were required to control intraocular pressure in 37% of patients. Ocular adverse events occurring in approximately 10 - 40% of patients in decreasing order of incidence were ocular/conjunctival hyperemia, reduced visual acuity, glaucoma, conjunctival hemorrhage, blurred vision, abnormal sensation in the eye, eye irritation, maculopathy, vitreous floaters, hypotony, pruritus, ptosis, increased tearing, vitreous hemorrhage, dry eye, eyelid edema, macular edema and visual disturbance.

Ocular adverse events occurring in approximately 5 - 9% of patients in decreasing order of incidence were eye discharge, photophobia, blepharitis, corneal edema, iris adhesions, choroidal detachment, diplopia, eye swelling, retinal detachment, photopsia, retinal hemorrhage and hyphema.

6.2 Clinical Trials Experience - Non-Ocular Events

The most frequently reported non-ocular adverse event was headache (33%). Other non-ocular adverse events occurring in approximately 5-20% of patients in decreasing order of incidence were nasopharyngitis, arthralgia, sinusitis, dizziness, pyrexia, upper respiratory tract infection, influenza, vomiting, nausea, cough, back pain, limb pain, and rash.

8 USE IN SPECIFIC POPULATIONS

8.1 Pregnancy

Risk Summary

Adequate and well-controlled studies with RETISERT have not been conducted in pregnant women to inform drug-associated risk. Animal reproduction studies have not been conducted with RETISERT. It is not known whether RETISERT can cause fetal harm when administered to a pregnant woman or can affect reproduction capacity. Corticosteroids have been shown to be teratogenic in laboratory animals when administered systemically at relatively low dosage levels. RETISERT should be used during pregnancy only if the potential benefit justifies the potential risk to the fetus.

In the US general population, the estimated background risk of major birth defects and miscarriage in clinically recognized pregnancies is 2% to 4% and 15% to 20%, respectively.

8.2 Lactation

Risk Summary

There are no data on the presence of RETISERT in human milk, the effects on the breastfed infant, or the effects on milk production. Systemically administered corticosteroids are present in human milk and can suppress growth, interfere with endogenous corticosteroid production, or cause other unwanted effects. Clinical or nonclinical lactation studies have not been conducted with RETISERT.

It is not known whether intravitreal treatment with RETISERT could result in sufficient systemic absorption to produce detectable quantities of fluocinolone acetonide in human milk, or affect breastfed infants or milk production.

The developmental and health benefits of breastfeeding should be considered along with the mother’s clinical need for RETISERT and any potential adverse effects on the breastfed child from RETISERT or from the underlying maternal condition.

8.4 Pediatric Use

Safety and effectiveness in pediatric patients below the age of 12 years have not been established.

8.5 Geriatric Use

No overall differences in safety and effectiveness have been observed between elderly and younger patients.

11 DESCRIPTION

RETISERT®(fluocinolone acetonide intravitreal implant) 0.59 mg is a sterile implant designed to release fluocinolone acetonide locally to the posterior segment of the eye at a nominal initial rate of 0.6 mcg/day, decreasing over the first month to a steady state between 0.3-0.4 mcg/day over approximately 30 months. The drug substance is the synthetic corticosteroid fluocinolone acetonide, represented by the following structural formula:

C24H30F2O6Mol. Wt. 452.50

Chemical Name: Pregna-1,4-diene-3,20-dione,6,9-difluoro-11,21-dihydroxy-16,17-[(1-methyl-ethylidene)bis(oxy)],(6α,11β ,16α)-.

Fluocinolone acetonide is a white crystalline powder, insoluble in water, and soluble in methanol. It has a melting point of 265-266ºC.

Each RETISERT consists of a tablet containing 0.59 mg of the active ingredient, Fluocinolone Acetonide, USP, and the following inactives: magnesium stearate, microcrystalline cellulose, and polyvinyl alcohol.

12 CLINICAL PHARMACOLOGY

12.1 Mechanism of Action

Corticosteroids inhibit the inflammatory response to a variety of inciting agents and probably delay or slow healing. They inhibit the edema, fibrin deposition, capillary dilation, leukocyte migration, capillary proliferation, fibroblast proliferation, deposition of collagen, and scar formation associated with inflammation.

There is no generally accepted explanation for the mechanism of action of ocular corticosteroids. However, corticosteroids are thought to act by the induction of phospholipase A2inhibitory proteins, collectively called lipocortins. It is postulated that these proteins control the biosynthesis of potent mediators of inflammation such as prostaglandins and leukotrienes by inhibiting the release of their common precursor arachidonic acid. Arachidonic acid is released from membrane phospholipids by phospholipase A2. Corticosteroids are capable of producing a rise in intraocular pressure.

12.3 Pharmacokinetics

In a subset of patients who received the intravitreal implant, and had blood samples taken at various times (weeks 1, 4 and 34) after implantation, plasma levels of fluocinolone acetonide were below the limit of detection (0.2 ng/mL) at all times. Aqueous and vitreous humor samples were assayed for fluocinolone acetonide in a further subset of patients. While detectable concentrations of fluocinolone acetonide were seen throughout the observation interval (up to 34 months), the concentrations were highly variable, ranging from below the limit of detection (0.2 ng/mL) to 589 ng/mL.

13 NONCLINICAL TOXICOLOGY

13.1 Carcinogenesis, Mutagenesis, Impairment of Fertility

Long-term animal studies have not been performed to determine the carcinogenic potential or the effect on fertility of RETISERT.

Fluocinolone acetonide was not genotoxic in vitro in the Ames test (S. typhimurium and E. coli), the mouse lymphoma TK assay, or in vivoin the mouse bone marrow micronucleus assay.

14 CLINICAL STUDIES

In two randomized, double-masked, multicenter controlled clinical trials, 224 patients with chronic (a one year or greater history) non-infectious uveitis affecting the posterior segment of one or both eyes were randomized to receive a 0.59 mg RETISERT. The primary efficacy endpoint in both trials was the rate of recurrence of uveitis affecting the posterior segment of the study eye in the 34 week pre-implantation period compared to the rate of recurrence in the 34 week post-implantation period. Uveitis recurrence rates at 1, 2, and 3 year post-implantation were also compared to the 34 week pre-implantation period.

Detailed results are shown in Table 1 below:

Table 1: Uveitis Recurrence Rates

TIME POINT | STUDY 1 | STUDY 2
TIME POINT | N=108 | N=116
TIME POINT | Uveitis Recurrence Rates^1,2 N (%)
34 Weeks Pre- implantation | 58 (53.7) | 46 (39.7)
34 Weeks Post- implantation | 2 (1.8) | 15 (12.9)
1 Year Post-implantation | 4 (3.7) | 15 (12.9)
2 Years Post-implantation | 11 (10.2) | 16 (13.8)
3 Years Post-implantation | 22 (20.4) | 20 (17.2)
3 Years^3Post- implantation | 33 (30.6) | 28 (24.1)

^1Recurrence of uveitis for all post-implantation time points was compared to the 34 weeks pre-implantation time point.

^2p-value <0.01 from McNemar’s χ^2test.

^3Results presented include imputed recurrences. Recurrences were imputed when a subject was not seen within 10 weeks of their final scheduled visit.

In assessing the effect of RETISERT on the corneal endothelial cell density in eyes that have been implanted for a minimum of 1 year, the results indicate that eyes containing the RETISERT implant for an average of 3.54 years had a lower mean corneal endothelial cell density (mean paired difference of -435 cells/mm^2) compared with non-implanted eyes (p<0.01).

16 HOW SUPPLIED/STORAGE AND HANDLING

The implant consists of a tablet encased in a silicone elastomer cup containing a release orifice and a polyvinyl alcohol membrane positioned between the tablet and the orifice. The silicone elastomer cup assembly is attached to a silicone elastomer suture tab with silicone adhesive. Each RETISERT is approximately 3 mm x 2 mm x 5 mm.

Each implant is stored in a clear polycarbonate case within a foil pouch within a Tyvek peelable overwrap. Each packaged implant is provided in a carton which includes the package insert.

NDC 24208-416-01 0.59 mg 1 count

Storage:Store in the original container at 15°C to 25°C (59°F to 77°F). Protect from freezing.

17 PATIENT COUNSELING INFORMATION

Patients should be advised to have ophthalmologic follow-up examinations of both eyes at appropriate intervals following implantation of RETISERT.

As with any surgical procedure, there is risk involved. Potential complications accompanying intraocular surgery to place RETISERT into the vitreous cavity may include, but are not limited to, the following: cataract formation, choroidal detachment, temporary decreased visual acuity, endophthalmitis, hypotony, increased intraocular pressure, exacerbation of intraocular inflammation, retinal detachment, vitreous hemorrhage, vitreous loss, and wound dehiscence.

Following implantation of RETISERT, nearly all patients will experience an immediate and temporary decrease in visual acuity in the implanted eye which lasts for approximately one to four weeks post-operatively.

Based on clinical trials with RETISERT, within 3 years post-implantation, approximately 77% of patients will require IOP lowering medications to control intraocular pressure and 37% of patients will require filtering procedures to control intraocular pressure [see Adverse Reactions (6.1)] .

Based on clinical trials with RETISERT, during the 3-year post-implantation period, nearly all phakic eyes are expected to develop cataracts and require cataract surgery.

Manufactured for:
Bausch & Lomb Americas Inc
Bridgewater, NJ 08807 USA
Manufactured by:
Bausch + Lomb Ireland Limited
Waterford, Ireland
RETISERT is a trademark of Bausch & Lomb Incorporated or its affiliates.
© 2025 Bausch & Lomb Incorporated or its affiliates

9028012

PACKAGE/LABEL PRINCIPAL DISPLAY PANEL

NDC24208-416-01

Rx only

Retisert®
(fluocinolone acetonide

intravitreal implant) 0.59 mg

STERILE

FOR INTRAVITREAL IMPLANTATION ONLY

Contents:One sterile Retisert®(fluocinolone acetonide intravitreal implant)
0.59 mg

Content sterile in unopened, undamaged package.

BAUSCH + LOMB